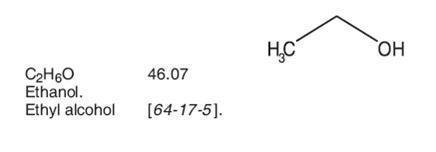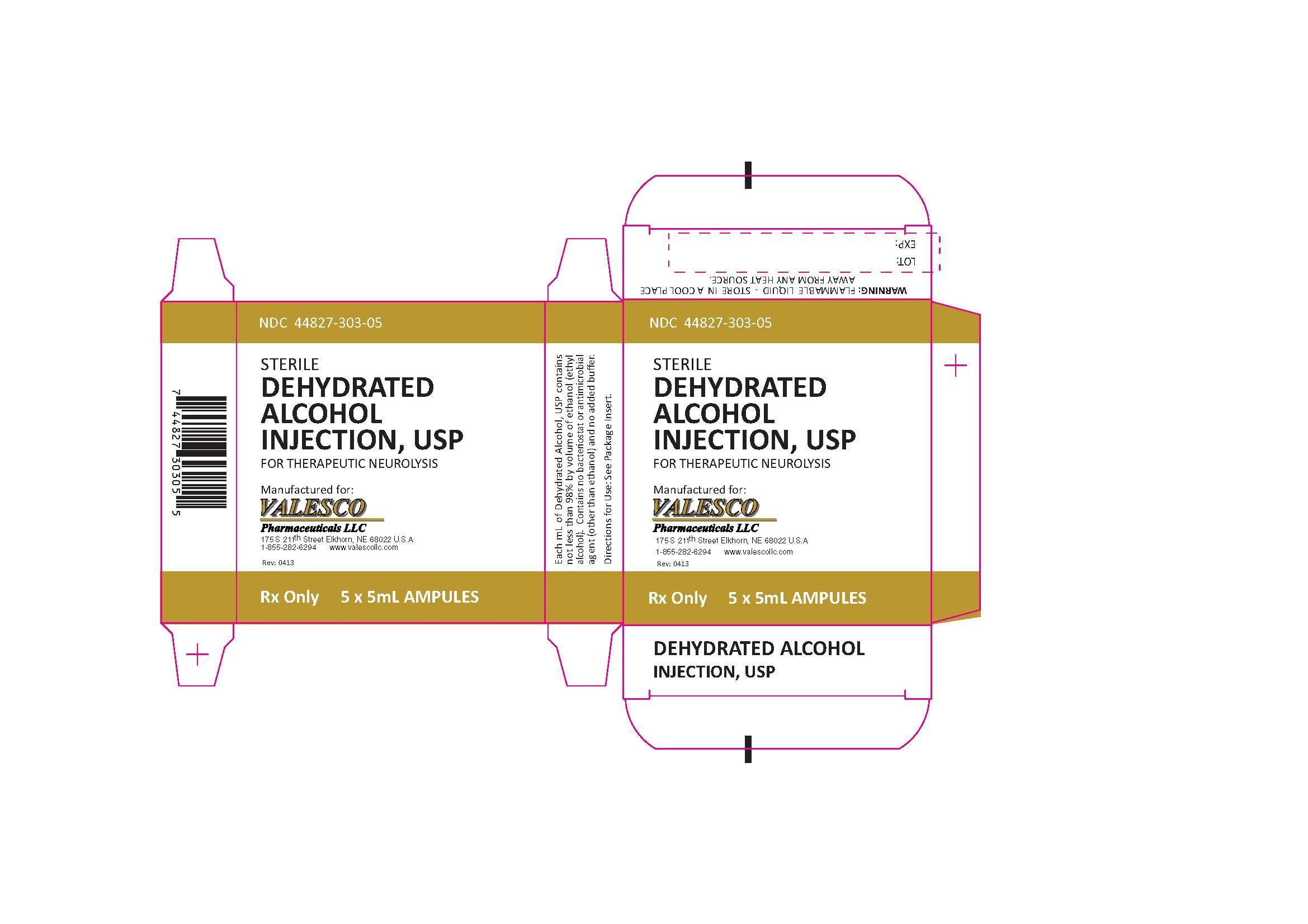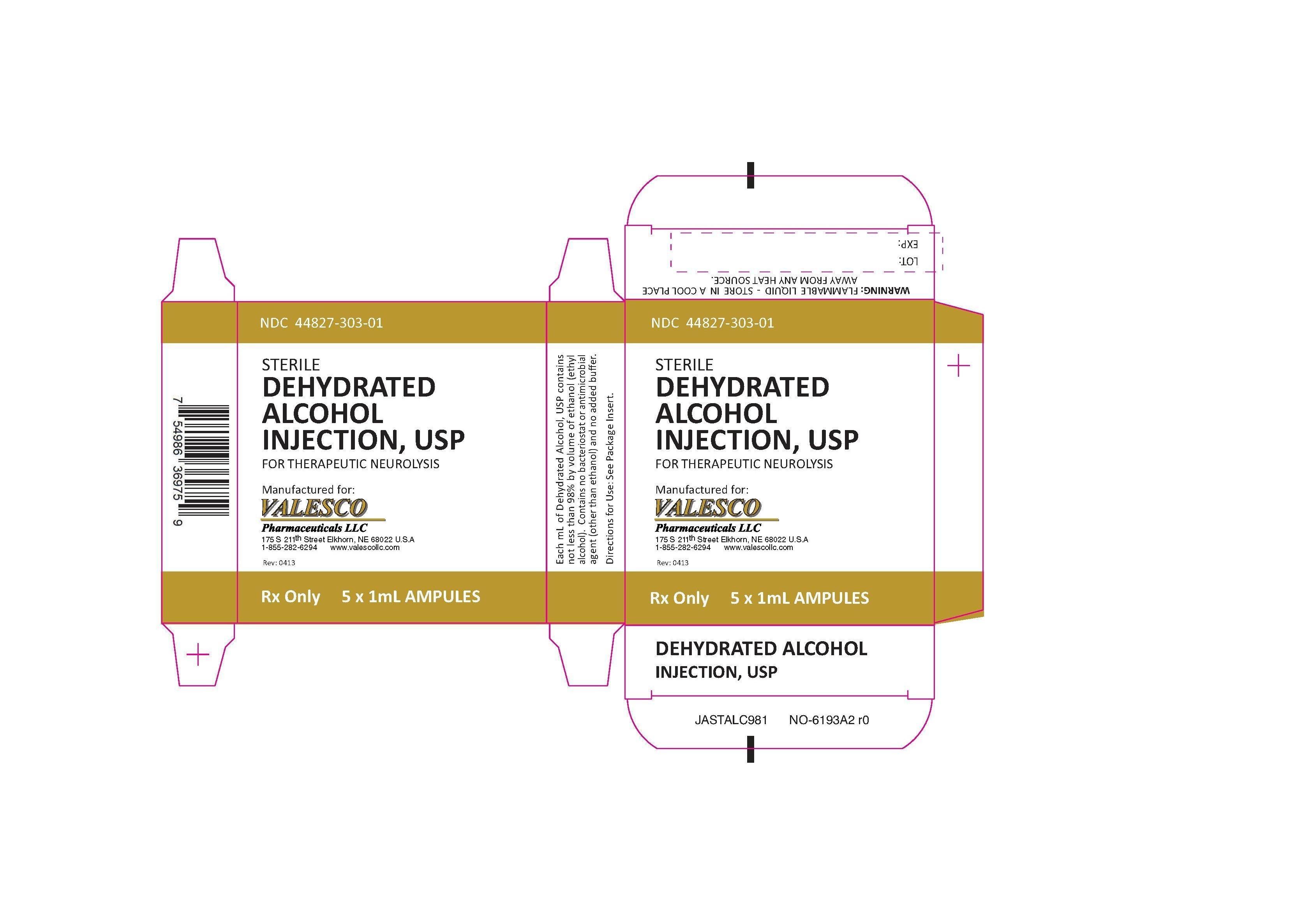 DRUG LABEL: Dehydrated Alcohol
NDC: 44827-303 | Form: SOLUTION
Manufacturer: Valesco Pharmaceuticals
Category: prescription | Type: HUMAN PRESCRIPTION DRUG LABEL
Date: 20140718

ACTIVE INGREDIENTS: ALCOHOL 0.98 mL/1 mL

DESCRIPTION

Dehydrated Alcohol Injection, USP consists of not less than 98% by volume of ethanol (ethyl alcohol). Dehydrated alcohol is hypobaric in relation to the cerebrospinal fluid. It is injected proximate to nerve tissues and into spinal subarachnoid spaces to produce degeneration of nerve function (neurolysis) for control of chronic pain.

The product contains no bacteriostat or antimicrobial agent (other than ethanol) and no added buffer.

Dehydrated alcohol is a clear, colorless liquid miscible with water and has the following structural formula:

CLINICAL PHARMACOLOGY

Alcohol produces injury to tissue cells by dehydration and precipitation of protoplasm. When alcohol is injected in close proximity to nerve tissues, it produces neuritis and nerve degeneration (neurolysis). Deliberate injury to selected spinal nerves, peripheral nerves, or ganglia by injection of alcohol results in more or less enduring block of sensory, motor and autonomic function.

The injection of alcohol used for therapeutic neurolysis involves amounts too small to produce significant systemic effects of ethanol.

Ninety to 98% of ethyl alcohol that enters the body is completely oxidized.

INDICATIONS AND USAGE

Dehydrated Alcohol Injection is indicated for therapeutic neurolysis of nerves or ganglia for the relief of intractable chronic pain in such conditions as inoperable cancer and trigeminal neuralgia (ticdouloureux), in patients for whom neurosurgical procedures are contraindicated. Relief of trigeminal neuralgia usually is only temporary. Other conditions for which injection of alcohol has been reported include glossopharyngeal neuralgia, angina pectoris and severe claudication due to peripheral vascular insufficiency. Alcohol concentrations of 40 to 50% (prepared by appropriate dilution of dehydrated alcohol) have been used for epidural or individual motor nerve injections to control certain manifestations of cerebral palsy and spastic paraplegia. Similar concentrations also have been injected for celiac plexus block to relieve pain of inoperable upper abdominal cancer, and have been injected intra-and subcutaneously for relief of intractable pruritus ani.

CONTRAINDICATIONS

Subarachnoid injection of dehydrated alcohol is contraindicated in patients receiving anticoagulants because of the danger of bleeding.

WARNINGS

Alcohol is a flammable liquid and should be kept cool and away from any heat source. Alcohol injections should be made with care to avoid unwanted tissue necrosis. Proper positioning of the patient is essential to control localization of injections of dehydrated alcohol (which is hypobaric) into the subarachnoid space.

PRECAUTIONS

Do not administer unless solution is clear and container is intact. Discard unused portion.

It is sometimes advisable to make a trial injection of procaine or other local anesthetic prior to alcohol injection as a means of confirming accurate placement of the needle, and to decrease pain experienced during the procedure. X-ray visualization for precise placement also may be advisable.

When used for selective sensory block within the subarachnoid space, it is essential to avoid contact of the alcohol with the anterior (motor) roots of the spinal nerve to be treated if motor paralysis is not desired. When peripheral nerves are injected, care should be taken that residual alcohol is not deposited along the needle track or in any other locations where tissue destruction is not wanted. Instances have been reported in which the pain resulting from post-injection neuritis was more severe than that existing before the injection.

Pregnancy

Pregnancy Category C: Animal reproduction studies have not been conducted with dehydrated alcohol. It is also not known whether dehydrated alcohol can cause fetal harm when given to a pregnant woman or can affect reproduction capacity. Dehydrated alcohol should be given to a pregnant woman only if clearly needed.

ADVERSE REACTIONS

The most commonly encountered side effects are post-injection neuritis with persistent pain, hyperesthesia and paresthesia. Subarachnoid neurolysis and lumbar sympathetic block may be followed by motor paralysis, bladder or rectal incontinence and impotence. Severe hypotension may follow celiac ganglion injection. Corneal anesthesia, meningitis or cranial nerve palsy may follow injection of the gasserian ganglion.

DRUG ABUSE AND DEPENDENCE

None known with this size and manner of presentation.

OVERDOSAGE

Excessive or faulty localization of injections may result in unwanted post-injection neuritis and/or tissue necrosis.

In such cases, efforts should be directed toward dilution of deposited alcohol when feasible, relief of pain with analgesics and surgical intervention if indicated.

Hypotension following celiac ganglion injection may be controlled with appropriate vasopressor agents. See PRECAUTIONS and ADVERSE REACTIONS.

DOSAGE AND ADMINISTRATION

The dosage of Dehydrated Alcohol Injection for therapeutic nerve or ganglion block varies from as little as 0.05 to 0.5 mL in trigeminal neuralgia to 0.5 to 1.0 mL per interspace for subarachnoid injections. Doses larger than 1.5 mL are seldom required. All injections should be made slowly and only after all steps have been taken to insure precise placement of the alcohol. A 1.0 mL tuberculin syringe is desirable to facilitate accurate measurement of the dose. Separate needles should be used for injection of successive interspaces or other sites. Since Dehydrated Alcohol Injection is hypobaric as compared to spinal fluid, proper positioning of the patient is essential to control localization of injections into the subarachnoid space.

When lesser concentrations of alcohol are used, larger volumes are usually injected. A dose of 2 mL of 45% alcohol has been used for injecting individual motor nerves, or from 1.5 to 4.0 mL for epidural injection in children with spastic cerebral palsy; 50 mL of 50% alcohol has been used for celiac plexus blockade.

The LD50 oral dose in rats is 13.7 g/kg.

Parenteral drug products should be inspected visually for particulate matter and discoloration prior to administration, whenever solution and container permit. See PRECAUTIONS.

HOW SUPPLIED

Dehydrated Alcohol Injection, USP

NDC 44827-303-01 1 mL Ampule Package of 5

NDC 44827-303-05 5 mL Ampule Package of 5

Store in a cool place away from any heat source.

Valesco Pharmaceuticals LLC

175 South 211th Street

Elkhorn, Nebraska 68022

Rev 04/13